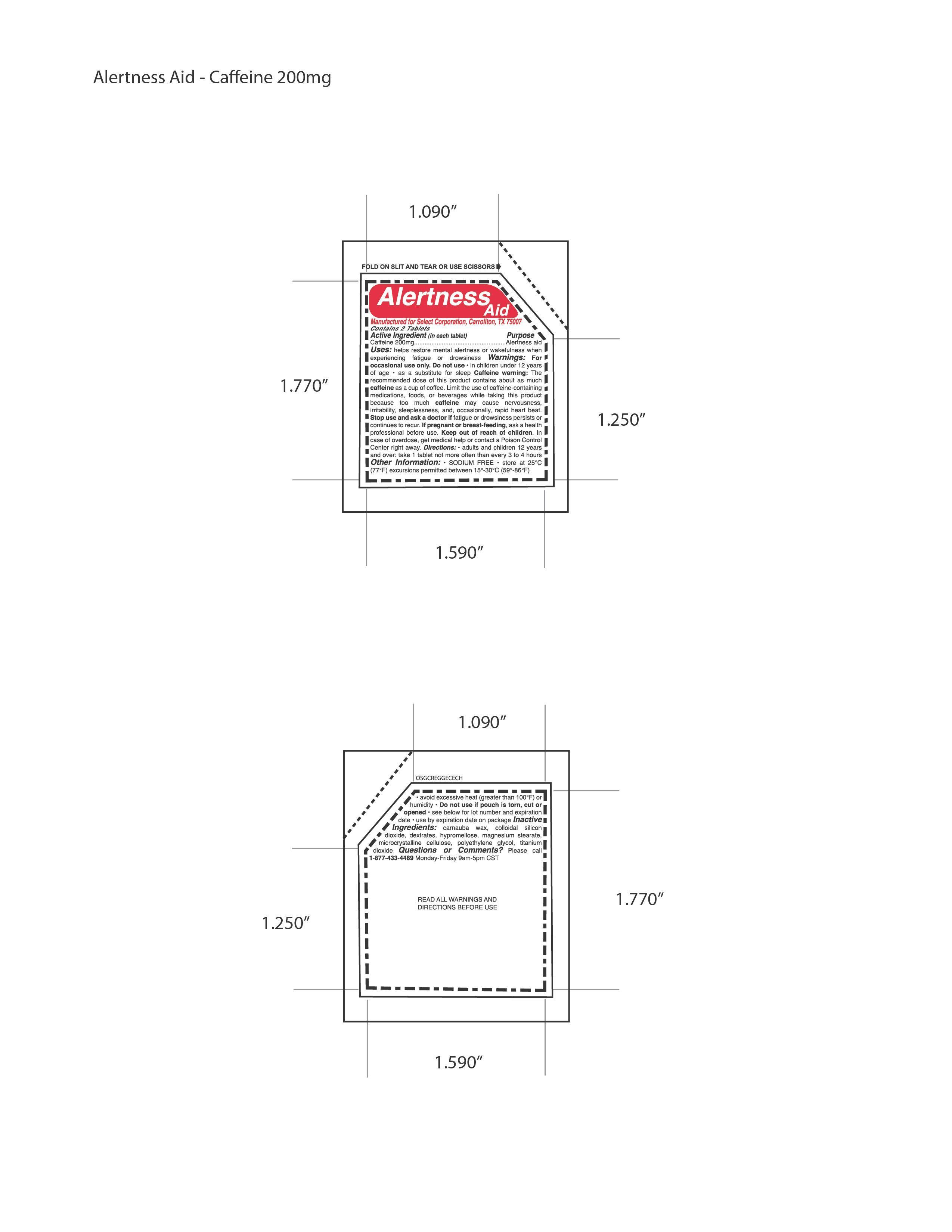 DRUG LABEL: Allertness Aid
                
NDC: 52904-470 | Form: TABLET
Manufacturer: Select Corporation
Category: otc | Type: HUMAN OTC DRUG LABEL
Date: 20121015

ACTIVE INGREDIENTS: CAFFEINE 200 mg/1 1
INACTIVE INGREDIENTS: TITANIUM DIOXIDE; SILICON DIOXIDE; CARNAUBA WAX; POLYETHYLENE GLYCOL 300; CELLULOSE, MICROCRYSTALLINE; MAGNESIUM STEARATE; DEXTRATES

Drug Facts

Active Ingredients Caffeine 200mg

PURPOSE

Alertness Aid

DOSAGE AND ADMINISTRATION

Directions: • adults and children 12 years
and over: take 1 tablet not more often than every 3 to 4 hours

INDICATIONS AND USAGE

Uses: helps restore mental alertness or wakefulness when
experiencing fatigue or drowsiness

Warnings: For
occasional use only. Do not use • in children under 12 years
of age • as a substitute for sleep Caffeine warning: The
recommended dose of this product contains about as much
caffeine as a cup of coffee. Limit the use of caffeine-containing
medications, foods, or beverages while taking this product
because too much caffeine may cause nervousness,
irritability, sleeplessness, and, occasionally, rapid heart beat.
Stop use and ask a doctor if fatigue or drowsiness persists or
continues to recur.

PREGNANCY OR BREAST FEEDING

If pregnant or
breast-feeding, ask a health professional before use.

KEEP OUT OF REACH OF CHILDREN.

Inactive
Ingredients: carnauba wax, colloidal silicon
dioxide, dextrates, hypromellose, magnesium stearate,
microcrystalline cellulose, polyethylene glycol, titanium
dioxide

PACKAGE LABEL

MM1